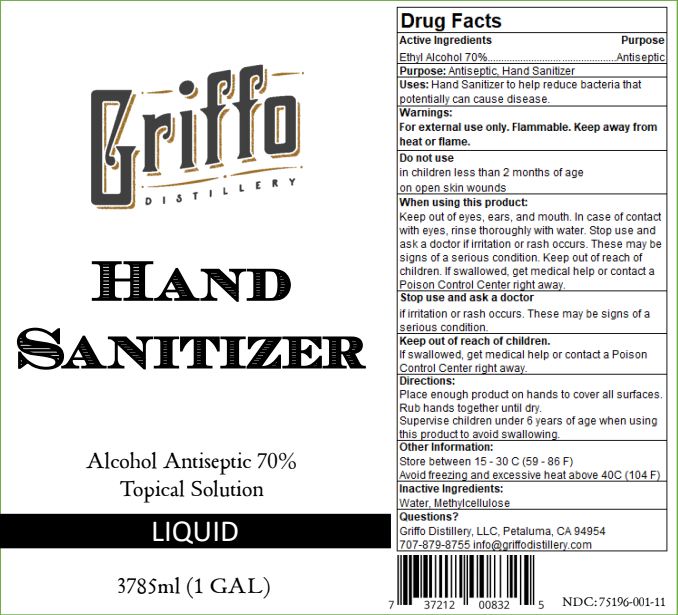 DRUG LABEL: Hand Sanitizer
NDC: 75196-001 | Form: GEL
Manufacturer: Griffo Distillery
Category: otc | Type: HUMAN OTC DRUG LABEL
Date: 20200414

ACTIVE INGREDIENTS: ALCOHOL 70 mL/100 mL
INACTIVE INGREDIENTS: METHYLCELLULOSE (4000 CPS) 1.3 mL/100 mL; WATER

Active Ingredient(s)

Alcohol 70% v/v. Purpose: Antiseptic

Purpose

Antiseptic, Hand Sanitizer

Use

Hand Sanitizer to help reduce bacteria that potentially can cause disease.

Warnings

For external use only. Flammable. Keep away from heat or flame.

Do not use

- in children less than 2 months of age
- on open skin wounds

WHEN USING

keep out of eyes, ears, and mouth. In case of contact with eyes, rinse eyes thoroughly with water.
Stop use and ask a doctor if irritation or rash occurs. These may be signs of a serious condition.
Keep out of reach of children. If swallowed, get medical help or contact a Poison Control Center right away.

Stop use and ask a doctor if irritation or rash occurs. These may be signs of a serious condition.

Keep out of reach of children. If swallowed, get medical help or contact a Poison Control Center right away.

Directions

- Place enough product on hands to cover all surfaces. Rub hands together until dry.
- Supervise children under 6 years of age when using this product to avoid swallowing.

Other information

- Store between 15-30 C (59-86 F)
- Avoid freezing and excessive heat above 40 C (104 F)

Inactive ingredients

Water, Methylcellulose

Questions:

Griffo Distillery LLC, Petaluma, CA 94954

(707) 879-8755 info@GriffoDistillery.com

Package Label - Principal Display Panel

3785 ml NDC: 75196-001-11